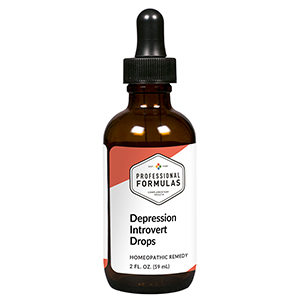 DRUG LABEL: Melancholy Drops Introvert
NDC: 63083-2016 | Form: LIQUID
Manufacturer: Professional Complementary Health Formulas
Category: homeopathic | Type: HUMAN OTC DRUG LABEL
Date: 20190815

ACTIVE INGREDIENTS: PASSIFLORA INCARNATA FLOWERING TOP 2 [hp_X]/59 mL; STRYCHNOS IGNATII SEED 3 [hp_X]/59 mL; PULSATILLA MONTANA WHOLE 4 [hp_X]/59 mL; SODIUM CHLORIDE 12 [hp_X]/59 mL; HUMAN CHOLECYSTOKININ-33 12 [hp_X]/59 mL; LIQUID PETROLEUM 60 [hp_X]/59 mL; SULFUR 60 [hp_X]/59 mL
INACTIVE INGREDIENTS: ALCOHOL; WATER

C16

ACTIVE INGREDIENTS

Passiflora incarnata 2X
Ignatia amara 3X, 6X, 12X, 60X
Pulsatilla 4X
Natrum muriaticum 12X
Cholecystokinin (CCK) 12X, 30X
Petroleum 60X
Sulphur 60X

QUESTIONS

Professional Formulas

PO Box 2034 Lake Oswego, OR 97035

INDICATIONS

For the temporary relief of sadness or fatigue, particularly in those with introverted personality.*

PURPOSE

*Claims based on traditional homeopathic practice, not accepted medical evidence. Not FDA evaluated.

WARNINGS

Persistent symptoms may be a sign of a serious condition. If symptoms persist or worsen, consult a doctor. Keep out of the reach of children. In case of overdose, get medical help or contact a poison control center right away. If pregnant or breastfeeding, ask a healthcare professional before use.

Keep out of the reach of children.

PREGNANCY OR BREAST FEEDING

If pregnant or breastfeeding, ask a healthcare professional before use.

DIRECTIONS

Place drops under tongue 30 minutes before/after meals. Adults and children 12 years and over: Take 10 drops up to 3 times per day. Consult a physician for use in children under 12 years of age.

OTHER INFORMATION

Tamper resistant. If seal is broken, do not use. After opening, close container tightly and store at room temperature away from heat.

INACTIVE INGREDIENTS

20% ethanol, purified water.

LABEL

Est 1985

Professional Formulas

Complementary Health

Melancholy Drops Introvert

Homeopathic Remedy

2 FL. OZ. (59 mL)